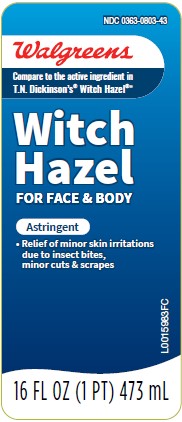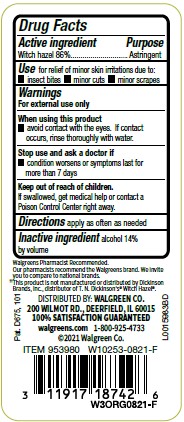 DRUG LABEL: Witch Hazel
NDC: 0363-0803 | Form: LIQUID
Manufacturer: Walgreen Co.
Category: otc | Type: HUMAN OTC DRUG LABEL
Date: 20260212

ACTIVE INGREDIENTS: WITCH HAZEL 860 mg/1 mL
INACTIVE INGREDIENTS: ALCOHOL

Walgreens 822.001/822AA
Witch Hazel

Active ingredient

Witch Hazel 86%

Purpose

Astringent

Use

for relief of minor skin irritations due to:

- insects bites
- minor cuts
- monor scrapes

Warnings

For external use only

When using this product

- avoid contact with the eyes. If contact occurs, rinse thoroughly with water.

Stop use and ask a doctor if

- condition worses or symptoms last for more than 7 days

Keep out of reach of children.

If swallowed, get medical help or contact a Poison Control Center right away.

Directions

apply as often as needed

Inactive ingredient

alcohol 14% by volume

Claims

Walgreens Pharmacist Recommended.

Our pharmacists recommend the Walgreens brand. We invite you to compare to national brands.

‡This product is not manufactured or distributed by Dickinson Brands, Inc., distributor of T. N. Dickinson'sWitch Hazel.*

adverse reactions

DISTRIBUTED BY: WALGREEN CO.

200 WILMOT RD., DEERFIELD, IL 60015

100% SATISFACTION GUARANTEED

walgreens.com 1-800-925-4733

©2021 Walgreen Co.

Pat. D675, 101

Principal Panel Display

NDC 0363-0803-43

Walgreens

Compare to the active ingredient in T. N. Dickinson's®Witch Hazel®‡

Witch Hazel

For Face & Body

Astringent

- Relief of minor skin irritations due to insect bites, minor cuts & scrapes

16 FL OZ (1 PT) 473 mL